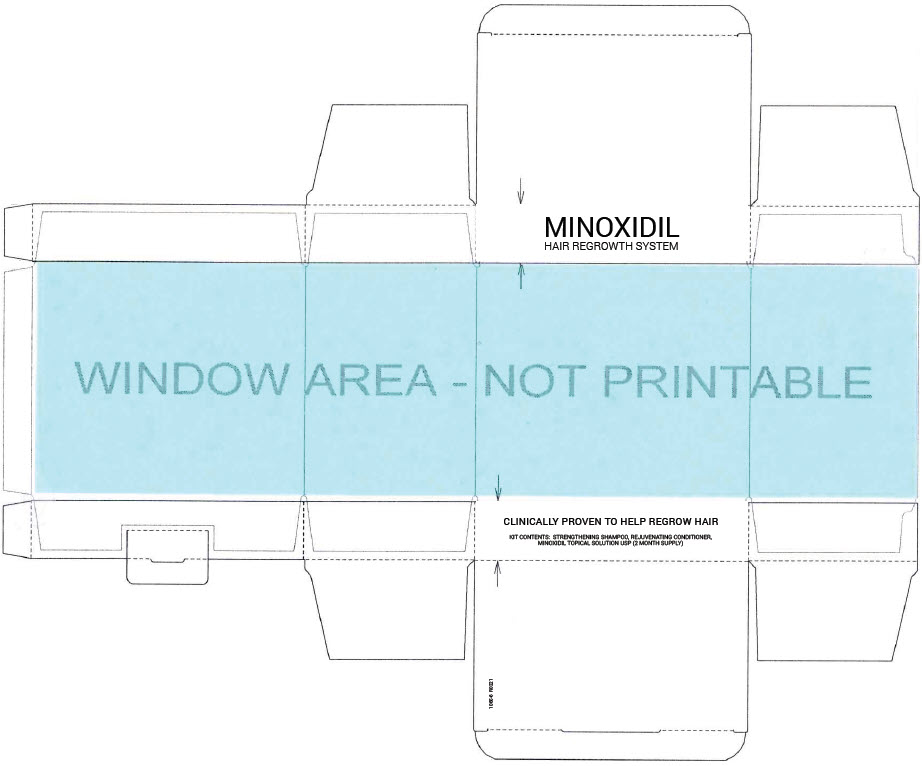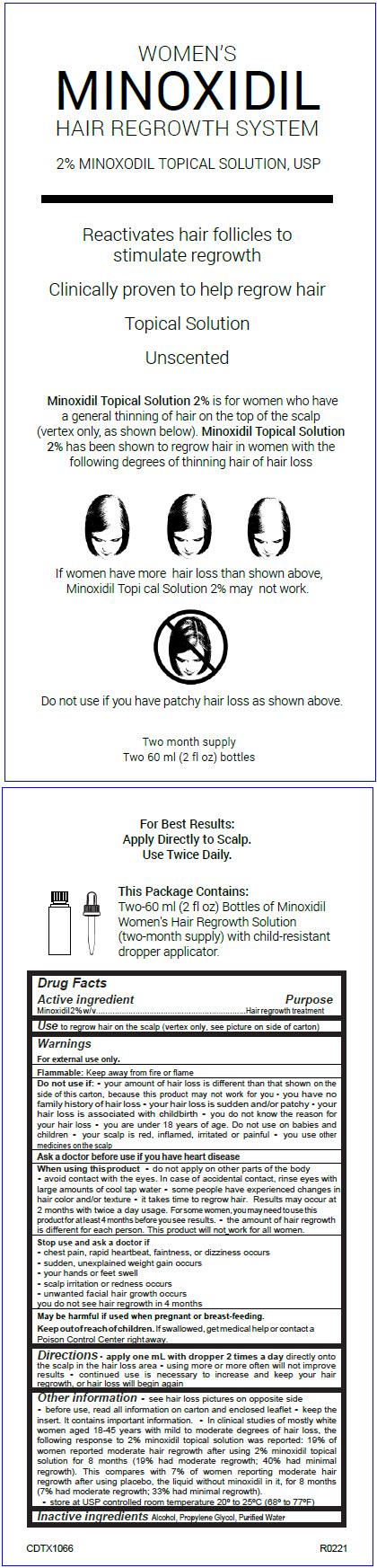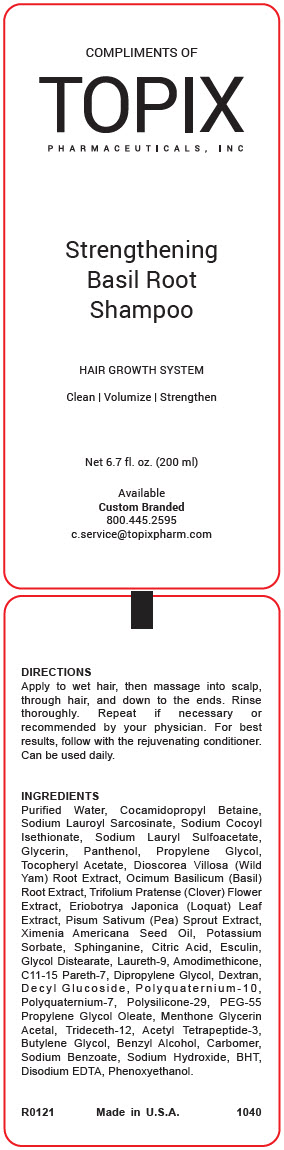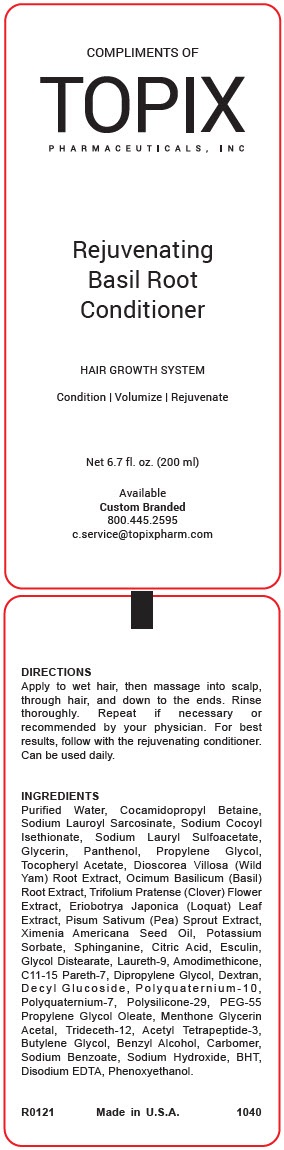 DRUG LABEL: Womens Minoxidil Hair Regrowth
								
NDC: 51326-166 | Form: KIT | Route: TOPICAL
Manufacturer: Topiderm, Inc
Category: otc | Type: HUMAN OTC DRUG LABEL
Date: 20241009

ACTIVE INGREDIENTS: MINOXIDIL 20 mg/1 mL
INACTIVE INGREDIENTS: ALCOHOL; PROPYLENE GLYCOL; WATER

Women's Minoxidil Hair Regrowth System

Drug Facts

Active ingredient

Minoxidil 2% w/v

Purpose

Hair regrowth treatment

Use

to regrow hair on the scalp (vertex only, see picture on side of carton)

Warnings

For external use only.

Flammable: Keep away from fire or flame

Do not use if

- your amount of hair loss is different than that shown on the side of this carton, because this product may not work for you
- you have no family history of hair loss
- your hair loss is sudden and/or patchy
- your hair loss is associated with childbirth
- you do not know the reason for your hair loss
- you are under 18 years of age. Do not use on babies and children
- your scalp is red, inflamed, irritated or painful
- you use other medicines on the scalp

Ask a doctor before use if you have heart disease

When using this product

- do not apply on other parts of the body
- avoid contact with the eyes. In case of accidental contact, rinse eyes with large amounts of cool tap water
- some people have experienced changes in hair color and/or texture
- it takes time to regrow hair. Results may occur at 2 months with twice a day usage. For some women, you may need to use this product for at least 4 months before you see results.
- the amount of hair regrowth is different for each person. This product will not work for all women.

Stop use and ask a doctor if

- chest pain, rapid heartbeat, faintness, or dizziness occurs
- sudden, unexplained weight gain occurs
- your hands or feet swell
- scalp irritation or redness occurs
- unwanted facial hair growth occurs

you do not see hair regrowth in 4 months

PREGNANCY OR BREAST FEEDING

May be harmful if used when pregnant or breast-feeding.

Keep out of reach of children. If swallowed, get medical help or contact a Poison Control Center right away.

Directions

- apply one mL with dropper 2 times a day directly onto the scalp in the hair loss area
- using more or more often will not improve results
- continued use is necessary to increase and keep your hair regrowth, or hair loss will begin again

Other information

- see hair loss pictures on opposite side
- before use, read all information on carton and enclosed leaflet
- keep the insert. It contains important information.
- In clinical studies of mostly white women aged 18-45 years with mild to moderate degrees of hair loss, the following response to 2% minoxidil topical solution was reported: 19% of women reported moderate hair regrowth after using 2% minoxidil topical solution for 8 months (19% had moderate regrowth; 40% had minimal regrowth). This compares with 7% of women reporting moderate hair regrowth after using placebo, the liquid without minoxidil in it, for 8 months (7% had moderate regrowth; 33% had minimal regrowth).
- store at USP controlled room temperature 20° to 25°C (68° to 77°F)

Inactive ingredients

Alcohol, Propylene Glycol, Purified Water

PRINCIPAL DISPLAY PANEL - Kit Carton

MINOXIDIL
HAIR REGROWTH SYSTEM

CLINICALLY PROVEN TO HELP REGROW HAIR

KIT CONTENTS: STRENGTHENING SHAMPOO, REJUVENATING CONDITIONER,
MINOXIDIL TOPICAL SOLUTION USP (2 MONTH SUPPLY)

PRINCIPAL DISPLAY PANEL - 2-60 mL Bottle Dropcard

WOMEN'S
MINOXIDIL
HAIR REGROWTH SYSTEM

2% MINOXODIL TOPICAL SOLUTION, USP

Reactivates hair follicles to
stimulate regrowth

Clinically proven to help regrow hair

Topical Solution

Unscented

Minoxidil Topical Solution 2% is for women who have
a general thinning of hair on the top of the scalp
(vertex only, as shown below). Minoxidil Topical Solution
2% has been shown to regrow hair in women with the
following degrees of thinning hair of hair loss

If women have more hair loss than shown above,
Minoxidil Topi cal Solution 2% may not work.

Do not use if you have patchy hair loss as shown above.

Two month supply
Two 60 ml (2 fl oz) bottles

PRINCIPAL DISPLAY PANEL - 200 mL Bottle Label-Shampoo

COMPLIMENTS OF
TOPIX
PHARMACEUTICALS, INC

Strengthening
Basil Root
Shampoo

HAIR GROWTH SYSTEM

Clean | Volumize | Strengthen

Net 6.7 fl. oz. (200 ml)

Available
Custom Branded
800.445.2595
c.service@topixpharm.com

PRINCIPAL DISPLAY PANEL - 200 mL Bottle Label-Conditioner

COMPLIMENTS OF
TOPIX
PHARMACEUTICALS, INC

Rejuvenating
Basil Root
Conditioner

HAIR GROWTH SYSTEM

Condition | Volumize | Rejuvenate

Net 6.7 fl. oz. (200 ml)

Available
Custom Branded
800.445.2595
c.service@topixpharm.com